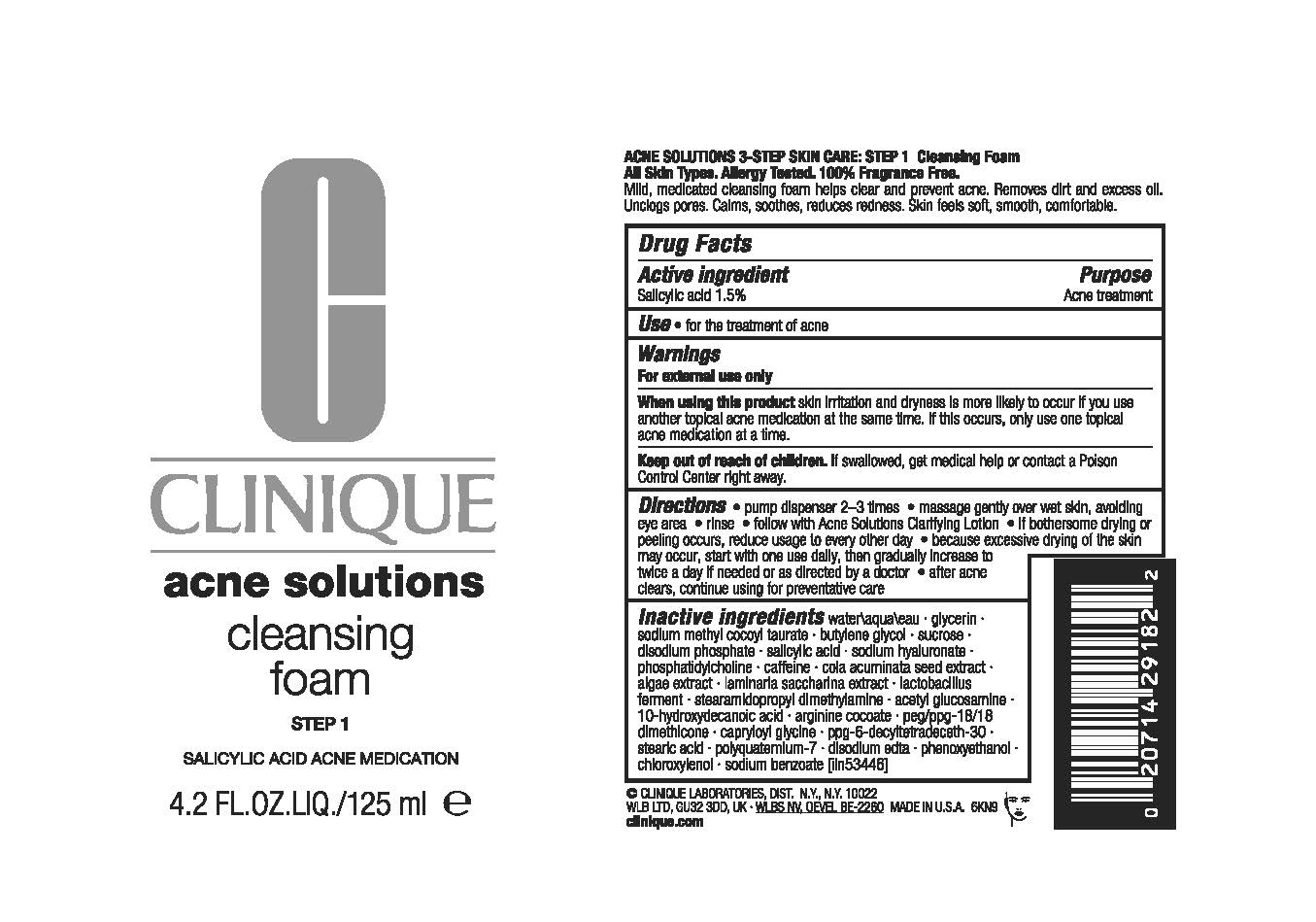 DRUG LABEL: CLINIQUE ACNE SOLUTIONS CLEANSING FOAM
NDC: 49527-119 | Form: LIQUID
Manufacturer: CLINIQUE LABORATORIES LLC
Category: otc | Type: HUMAN OTC DRUG LABEL
Date: 20250313

ACTIVE INGREDIENTS: SALICYLIC ACID 15 mg/1 mL
INACTIVE INGREDIENTS: PORPHYRIDIUM PURPUREUM; PEG/PPG-18/18 DIMETHICONE; WATER; GLYCERIN; BUTYLENE GLYCOL; SODIUM METHYL COCOYL TAURATE; SUCROSE; SODIUM PHOSPHATE, DIBASIC, ANHYDROUS; ARGININE COCOATE; SACCHARINA LATISSIMA; CAFFEINE; COLA ACUMINATA SEED; HYALURONATE SODIUM; STEARAMIDOPROPYL DIMETHYLAMINE; N-ACETYLGLUCOSAMINE; CAPRYLOYL GLYCINE; 10-HYDROXYDECANOIC ACID; POLYQUATERNIUM-7 (70/30 ACRYLAMIDE/DADMAC; 1600000 MW); STEARIC ACID; EDETATE DISODIUM ANHYDROUS; PHENOXYETHANOL; CHLOROXYLENOL; SODIUM BENZOATE; PHOSPHATIDYLCHOLINE, SOYBEAN

CLINIQUE ACNE SOLUTIONS CLEANSING FOAM

Active ingredient

Salicylic acid 1.5%

Purpose

Acne treatment

Use

- for the treatment of acne

Warnings

For external use only

When using this product

skin irritation and dryness is more likely to occur if you use another topical acne medication at the same time. If this occurs, only use one topical acne medication at a time.

Keep out of reach of childeren.

If swallowed, get medical help or contact a Poison Control Center right away.

Directions

- pump dispenser 2-3 times
- massage gently over wet skin, avoiding eye area
- rinse
- follow with Acne Solutions Clarifying Lotion
- if bothersome drying or peeling occurs, reduce usage to every other day
- because excessive drying of the skin may occur, start with one use daily, then gradually increase to twice a day if needed or as directed by a doctor
- after acne clears, continue using for preventative care

Inactive ingredients

water\aqua\eau,glycerin,sodium methyl cocoyl taurate,butylene glycol,sucrose,disodium phosphate,salicylic acid,sodium hyaluronate,phosphatidylcholine,caffeine,cola acuminata seed extract,algae extract,laminaria saccharina extract,lactobacillus ferment,stearamidopropyl dimethylamine,acetyl glucosamine,10-hydroxydecanoic acid,arginine cocoate,peg/ppg-18/18 dimethicone,capryloyl glycine,ppg-6-decyltetradeceth-30,stearic acid,polyquaternium-7,disodium edta,phenoxyethanol,chloroxylenol,sodium benzoate <iln53446>

PRINCIPAL DISPLAY PANEL - 125 ml Bottle Label

CLINIQUE
acne solutions

cleansing
foam

STEP 1

SALICYLIC ACID ACNE MEDICATION

4.2 FL.OZ.LIQ./125 ml e